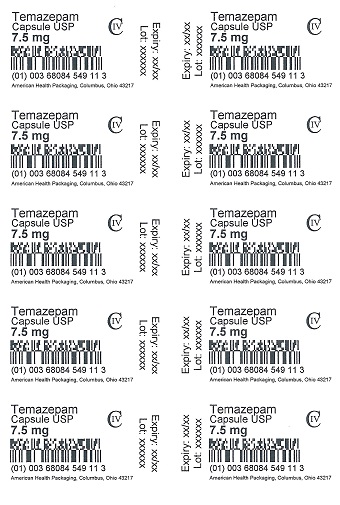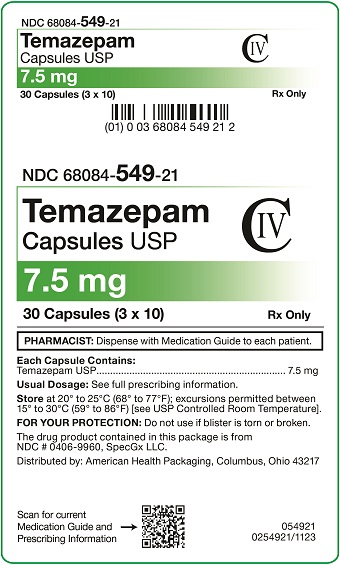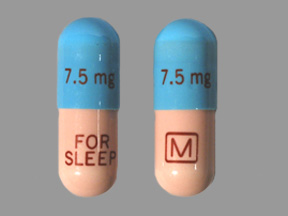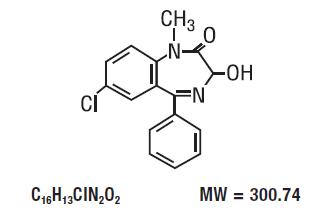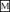 DRUG LABEL: Temazepam
NDC: 68084-549 | Form: CAPSULE
Manufacturer: American Health Packaging
Category: prescription | Type: HUMAN PRESCRIPTION DRUG LABEL
Date: 20251113
DEA Schedule: CIV

ACTIVE INGREDIENTS: TEMAZEPAM 7.5 mg/1 1
INACTIVE INGREDIENTS: FD&C BLUE NO. 1; FD&C RED NO. 3; GELATIN, UNSPECIFIED; LACTOSE MONOHYDRATE; MAGNESIUM STEARATE; FERRIC OXIDE RED; TITANIUM DIOXIDE; BUTYL ALCOHOL; SHELLAC; ALCOHOL; ETHYL ACETATE

Temazepam Capsules USP CIV
8254921/1123
Rx only

WARNING: RISKS FROM CONCOMITANT USE WITH OPIOIDS; ABUSE, MISUSE, AND ADDICTION; and DEPENDENCE AND WITHDRAWAL REACTIONS

- Concomitant use of benzodiazepines and opioids may result in profound sedation, respiratory depression, coma, and death. Reserve concomitant prescribing of these drugs in patients for whom alternative treatment options are inadequate. Limit dosages and durations to the minimum required. Follow patients for signs and symptoms of respiratory depression and sedation (see WARNINGS and PRECAUTIONS).
- The use of benzodiazepines, including temazepam capsules, exposes users to risks of abuse, misuse, and addiction, which can lead to overdose or death. Abuse and misuse of benzodiazepines commonly involve concomitant use of other medications, alcohol, and/or illicit substances, which is associated with an increased frequency of serious adverse outcomes. Before prescribing temazepam capsules and throughout treatment, assess each patient’s risk for abuse, misuse, and addiction (see WARNINGS).
- The continued use of benzodiazepines, including temazepam capsules, may lead to clinically significant physical dependence. The risks of dependence and withdrawal increase with longer treatment duration and higher daily dose. Abrupt discontinuation or rapid dosage reduction of temazepam capsules after continued use may precipitate acute withdrawal reactions, which can be life-threatening. To reduce the risk of withdrawal reactions, use a gradual taper to discontinue temazepam capsules or reduce the dosage (see DOSAGE AND ADMINISTRATION and WARNINGS).

DESCRIPTION

Temazepam Capsules USP are benzodiazepine hypnotic agents. The chemical name is 7-chloro-1,3-dihydro-3-hydroxy-1-methyl-5-phenyl-2 H-1,4-benzodiazepin-2-one, and the structural formula is:

Temazepam is a white, crystalline substance, very slightly soluble in water and sparingly soluble in alcohol USP.

Temazepam Capsules USP, 7.5 mg, 15 mg, 22.5 mg, and 30 mg, are for oral administration.

7.5 mg, 15 mg, 22.5 mg, and 30 mg Capsules
Active Ingredient:temazepam USP

7.5 mg Capsules
Inactive Ingredients: FD&C Blue #1, FD&C Red #3, gelatin, lactose, magnesium stearate, red iron oxide, titanium dioxide.

May also include: n-butyl alcohol, iron oxide red, shellac, shellac glaze, SD-35A alcohol.

15 mg Capsules
Inactive Ingredients: FD&C Blue #1, FD&C Red #3, gelatin, lactose, magnesium stearate, red iron oxide, titanium dioxide.

May also include: n-butyl alcohol, FD&C Blue #1/Brilliant Blue FCF Aluminum Lake, iron oxide red, isopropyl alcohol, propylene glycol, shellac, shellac glaze, SD-35A alcohol, SD-45 alcohol.

22.5 mg Capsules
Inactive Ingredients: FD&C Blue #1, FD&C Red #3, gelatin, lactose, magnesium stearate, red iron oxide, titanium dioxide.

May also include: n-butyl alcohol, FD&C Blue #1/Brilliant Blue FCF Aluminum Lake, iron oxide red, isopropyl alcohol, propylene glycol, shellac, shellac glaze, SD-35A alcohol, SD-45 alcohol.

30 mg Capsules
Inactive Ingredients: FD&C Blue #1, FD&C Red #3, gelatin, lactose, magnesium stearate, red iron oxide, titanium dioxide.

May also include: n-butyl alcohol, FD&C Blue #1/Brilliant Blue FCF Aluminum Lake, iron oxide red, isopropyl alcohol, propylene glycol, shellac, shellac glaze, SD-35A alcohol, SD-45 alcohol.

CLINICAL PHARMACOLOGY

Pharmacokinetics

In a single and multiple dose absorption, distribution, metabolism, and excretion (ADME) study, using^3H labeled drug, Restoril (temazepam) was well absorbed and found to have minimal (8%) first pass metabolism. There were no active metabolites formed and the only significant metabolite present in blood was the O-conjugate. The unchanged drug was 96% bound to plasma proteins. The blood level decline of the parent drug was biphasic with the short half-life ranging from 0.4 to 0.6 hours and the terminal half-life from 3.5 to 18.4 hours (mean 8.8 hours), depending on the study population and method of determination. Metabolites were formed with a half-life of 10 hours and excreted with a half-life of approximately 2 hours. Thus, formation of the major metabolite is the rate limiting step in the biodisposition of temazepam. There is no accumulation of metabolites. A dose-proportional relationship has been established for the area under the plasma concentration/time curve over the 15 to 30 mg dose range.

Temazepam was completely metabolized through conjugation prior to excretion; 80% to 90% of the dose appeared in the urine. The major metabolite was the O-conjugate of temazepam (90%); the O-conjugate of N-desmethyl temazepam was a minor metabolite (7%).

Bioavailability, Induction, and Plasma Levels

Following ingestion of a 30 mg Restoril capsule, measurable plasma concentrations were achieved 10 to 20 minutes after dosing with peak plasma levels ranging from 666 to 982 ng/mL (mean 865 ng/mL) occurring approximately 1.2 to 1.6 hours (mean 1.5 hours) after dosing.

In a 7 day study, in which subjects were given a 30 mg Restoril capsule 1 hour before retiring, steady-state (as measured by the attainment of maximal trough concentrations) was achieved by the third dose. Mean plasma levels of temazepam (for days 2 to 7) were 260±210 ng/mL at 9 hours and 75±80 ng/mL at 24 hours after dosing. A slight trend toward declining 24 hour plasma levels was seen after day 4 in the study, however, the 24 hour plasma levels were quite variable.

At a dose of 30 mg once-a-day for 8 weeks, no evidence of enzyme induction was found in man.

Elimination Rate of Benzodiazepine Hypnotics and Profile of Common Untoward Effects

The type and duration of hypnotic effects and the profile of unwanted effects during administration of benzodiazepine hypnotics may be influenced by the biologic half-life of the administered drug and for some hypnotics, the half-life of any active metabolites formed. Benzodiazepine hypnotics have a spectrum of half-lives from short (<4 hours) to long (>20 hours). When half-lives are long, drug (and for some drugs their active metabolites) may accumulate during periods of nightly administration and be associated with impairments of cognitive and/or motor performance during waking hours; the possibility of interaction with other psychoactive drugs or alcohol will be enhanced. In contrast, if half-lives are shorter, drug (and, where appropriate, its active metabolites) will be cleared before the next dose is ingested, and carry-over effects related to excessive sedation or CNS depression should be minimal or absent. However, during nightly use for an extended period, pharmacodynamic tolerance or adaptation to some effects of benzodiazepine hypnotics may develop. If the drug has a short elimination half-life, it is possible that a relative deficiency of the drug, or, if appropriate, its active metabolites (i.e., in relationship to the receptor site) may occur at some point in the interval between each night's use. This sequence of events may account for 2 clinical findings reported to occur after several weeks of nightly use of rapidly eliminated benzodiazepine hypnotics, namely, increased wakefulness during the last third of the night, and the appearance of increased signs of daytime anxiety.

Controlled Trials Supporting Efficacy

Restoril improved sleep parameters in clinical studies. Residual medication effects (“hangover”) were essentially absent. Early morning awakening, a particular problem in the geriatric patient, was significantly reduced.

Patients with chronic insomnia were evaluated in 2 week, placebo controlled sleep laboratory studies with Restoril at doses of 7.5 mg, 15 mg, and 30 mg, given 30 minutes prior to bedtime. There was a linear dose-response improvement in total sleep time and sleep latency, with significant drug-placebo differences at 2 weeks occurring only for total sleep time at the 2 higher doses, and for sleep latency only at the highest dose.

In these sleep laboratory studies, REM sleep was essentially unchanged and slow wave sleep was decreased. No measurable effects on daytime alertness or performance occurred following Restoril treatment or during the withdrawal period, even though a transient sleep disturbance in some sleep parameters was observed following withdrawal of the higher doses. There was no evidence of tolerance development in the sleep laboratory parameters when patients were given Restoril nightly for at least 2 weeks.

In addition, normal subjects with transient insomnia associated with first night adaptation to the sleep laboratory were evaluated in 24 hour, placebo controlled sleep laboratory studies with Restoril at doses of 7.5 mg, 15 mg, and 30 mg, given 30 minutes prior to bedtime. There was a linear dose-response improvement in total sleep time, sleep latency and number of awakenings, with significant drug-placebo differences occurring for sleep latency at all doses, for total sleep time at the 2 higher doses and for number of awakenings only at the 30 mg dose.

INDICATIONS AND USAGE

Temazepam Capsules USP are indicated for the short-term treatment of insomnia (generally 7 to 10 days).

For patients with short-term insomnia, instructions in the prescription should indicate that Temazepam Capsules USP should be used for short periods of time (7 to 10 days).

The clinical trials performed in support of efficacy were 2 weeks in duration with the final formal assessment of sleep latency performed at the end of treatment.

WARNINGS

Risks from Concomitant Use with Opioids
Concomitant use of benzodiazepines, including temazepam capsules, and opioids may result in profound sedation, respiratory depression, coma, and death. Because of these risks, reserve concomitant prescribing of these drugs for use in patients for whom alternative treatment options are inadequate.

Observational studies have demonstrated that concomitant use of opioid analgesics and benzodiazepines increases the risk of drug-related mortality compared to use of opioids alone. If a decision is made to prescribe temazepam capsules concomitantly with opioids, prescribe the lowest effective dosages and minimum durations of concomitant use, and follow patients closely for signs and symptoms of respiratory depression and sedation. In patients already receiving an opioid analgesic, prescribe a lower initial dose of temazepam capsules than indicated in the absence of an opioid and titrate based on clinical response. If an opioid is initiated in a patient already taking temazepam capsules, prescribe a lower initial dose of the opioid and titrate based upon clinical response.

Advise both patients and caregivers about the risks of respiratory depression and sedation when temazepam capsules are used with opioids. Advise patients not to drive or operate heavy machinery until the effects of concomitant use with the opioid have been determined (see PRECAUTIONS, Drug Interactions).

Abuse, Misuse, and Addiction
The use of benzodiazepines, including temazepam capsules, exposes users to the risks of abuse, misuse, and addiction, which can lead to overdose or death. Abuse and misuse of benzodiazepines often (but not always) involve the use of doses greater than the maximum recommended dosage and commonly involve concomitant use of other medications, alcohol, and/or illicit substances, which is associated with an increased frequency of serious adverse outcomes, including respiratory depression, overdose, or death (see DRUG ABUSE AND DEPENDENCE, Abuse).

Before prescribing temazepam capsules and throughout treatment, assess each patient’s risk for abuse, misuse, and addiction (e.g., using a standardized screening tool). Use of temazepam capsules, particularly in patients at elevated risk, necessitates counseling about the risks and proper use of temazepam capsules along with monitoring for signs and symptoms of abuse, misuse, and addiction. Prescribe the lowest effective dosage; avoid or minimize concomitant use of CNS depressants and other substances associated with abuse, misuse, and addiction (e.g., opioid analgesics, stimulants); and advise patients on the proper disposal of unused drug. If a substance use disorder is suspected, evaluate the patient and institute (or refer them for) early treatment, as appropriate.

Dependence and Withdrawal Reactions
To reduce the risk of withdrawal reactions, use a gradual taper to discontinue temazepam capsules or reduce the dosage (a patient-specific plan should be used to taper the dose) (see DOSAGE AND ADMINISTRATION, Discontinuation or Dosage Reduction of Temazepam Capsules).

Patients at an increased risk of withdrawal adverse reactions after benzodiazepine discontinuation or rapid dosage reduction include those who take higher dosages, and those who have had longer durations of use.

Acute Withdrawal Reactions
The continued use of benzodiazepines, including temazepam capsules, may lead to clinically significant physical dependence. Abrupt discontinuation or rapid dosage reduction of temazepam capsules after continued use, or administration of flumazenil (a benzodiazepine antagonist) may precipitate acute withdrawal reactions, which can be life-threatening (e.g., seizures) (see DRUG ABUSE AND DEPENDENCE, Dependence).

Protracted Withdrawal Syndrome
In some cases, benzodiazepine users have developed a protracted withdrawal syndrome with withdrawal symptoms lasting weeks to more than 12 months (see DRUG ABUSE AND DEPENDENCE, Dependence).

Sleep disturbance may be the presenting manifestation of an underlying physical and/or psychiatric disorder. Consequently, a decision to initiate symptomatic treatment of insomnia should only be made after the patient has been carefully evaluated. The failure of insomnia to remit after 7 to 10 days of treatment may indicate the presence of a primary psychiatric and/or medical illness that should be evaluated. Worsening of insomnia may be the consequence of an unrecognized psychiatric or physical disorder as may the emergence of new abnormalities of thinking or behavior. Such abnormalities have also been reported to occur in association with the use of drugs with central nervous system depressant activity, including those of the benzodiazepine class. Because some of the worrisome adverse effects of benzodiazepines, including temazepam capsules, appear to be dose related (see PRECAUTIONSand DOSAGE AND ADMINISTRATION), it is important to use the lowest possible effective dose. Elderly patients are especially at risk.

Some of these changes may be characterized by decreased inhibition, e.g., aggressiveness and extroversion that seem out of character, similar to that seen with alcohol. Other kinds of behavioral changes can also occur, for example, bizarre behavior, agitation, hallucinations, and depersonalization. Complex behaviors such as “sleep-driving” (i.e., driving while not fully awake after ingestion of a sedative-hypnotic, with amnesia for the event) have been reported. These events can occur in sedative-hypnotic-naïve as well as in sedative-hypnotic-experienced persons. Although behaviors such as “sleep-driving” may occur with temazepam capsules alone at therapeutic doses, the use of alcohol and other CNS depressants with temazepam capsules appear to increase the risk of such behaviors, as does the use of temazepam capsules at doses exceeding the maximum recommended dose. Due to the risk to the patient and the community, discontinuation of temazepam capsules should be strongly considered for patients who report a “sleep-driving” episode. Other complex behaviors (e.g., preparing and eating food, making phone calls, or having sex) have been reported in patients who are not fully awake after taking a sedative-hypnotic. As with “sleep-driving”, patients usually do not remember these events. Amnesia and other neuro-psychiatric symptoms may occur unpredictably. In primarily depressed patients, worsening of depression, including suicidal thinking has been reported in association with the use of sedative/hypnotics.

It can rarely be determined with certainty whether a particular instance of the abnormal behaviors listed above is drug induced, spontaneous in origin, or a result of an underlying psychiatric or physical disorder. Nonetheless, the emergence of any new behavioral sign or symptom of concern requires careful and immediate evaluation.

Because temazepam capsules can cause drowsiness and a decreased level of consciousness, patients, particularly the elderly, are at higher risk of falls.

Severe Anaphylactic and Anaphylactoid Reactions
Rare cases of angioedema involving the tongue, glottis or larynx have been reported in patients after taking the first or subsequent doses of sedative-hypnotics, including temazepam capsules. Some patients have had additional symptoms such as dyspnea, throat closing, or nausea and vomiting that suggest anaphylaxis. Some patients have required medical therapy in the emergency department. If angioedema involves the tongue, glottis or larynx, airway obstruction may occur and be fatal. Patients who develop angioedema after treatment with temazepam capsules should not be rechallenged with the drug.

Neonatal Sedation and Withdrawal Syndrome
Use of temazepam capsules late in pregnancy can result in sedation (respiratory depression, lethargy, hypotonia) and/or withdrawal symptoms (hyperreflexia, irritability, restlessness, tremors, inconsolable crying, and feeding difficulties) in the neonate (see PRECAUTIONS, Pregnancy). Monitor neonates exposed to temazepam capsules during pregnancy or labor for signs of sedation and monitor neonates exposed to temazepam capsules during pregnancy for signs of withdrawal; manage these neonates accordingly.

PRECAUTIONS

General

Since the risk of the development of oversedation, dizziness, confusion, and/or ataxia increases substantially with larger doses of benzodiazepines in elderly and debilitated patients, 7.5 mg of temazepam capsules are recommended as the initial dosage for such patients.

Temazepam capsules should be administered with caution in severely depressed patients or those in whom there is any evidence of latent depression; it should be recognized that suicidal tendencies may be present and protective measures may be necessary.

The usual precautions should be observed in patients with impaired renal or hepatic function and in patients with chronic pulmonary insufficiency.

If temazepam capsules are to be combined with other drugs having known hypnotic properties or CNS-depressant effects, consideration should be given to potential additive effects.

The possibility of a synergistic effect exists with the co-administration of temazepam capsules and diphenhydramine. One case of stillbirth at term has been reported 8 hours after a pregnant patient received temazepam capsules and diphenhydramine. A cause and effect relationship has not yet been determined (see PRECAUTIONS, Pregnancy) .

Information for Patients

Advise the patient to read the FDA approved patient labeling (Medication Guide).

Risks from Concomitant Use with Opioids
Advise both patients and caregivers about the risks of potentially fatal respiratory depression and sedation when temazepam capsules are used with opioids and not to use such drugs concomitantly unless supervised by a healthcare provider. Advise patients not to drive or operate heavy machinery until the effects of concomitant use with the opioid have been determined (see WARNINGS, Risks from Concomitant Use with Opioidsand PRECAUTIONS, Drug Interactions).

Abuse, Misuse, and Addiction
Inform patients that the use of temazepam capsules, even at recommended dosages, exposes users to risks of abuse, misuse, and addiction, which can lead to overdose and death, especially when used in combination with other medications (e.g., opioid analgesics), alcohol, and/or illicit substances. Inform patients about the signs and symptoms of benzodiazepine abuse, misuse, and addiction; to seek medical help if they develop these signs and/or symptoms; and on the proper disposal of unused drug (see WARNINGS, Abuse, Misuse, and Addictionand DRUG ABUSE AND DEPENDENCE).

Withdrawal Reactions
Inform patients that the continued use of temazepam capsules may lead to clinically significant physical dependence and that abrupt discontinuation or rapid dosage reduction of temazepam capsules may precipitate acute withdrawal reactions, which can be life-threatening. Inform patients that in some cases, patients taking benzodiazepines have developed a protracted withdrawal syndrome with withdrawal symptoms lasting weeks to more than 12 months. Instruct patients that discontinuation or dosage reduction of temazepam capsules may require a slow taper (see WARNINGS, Dependence and Withdrawal Reactionsand DRUG ABUSE AND DEPENDENCE).

“Sleep-Driving” and Other Complex Behaviors
There have been reports of people getting out of bed after taking a sedative-hypnotic and driving their cars while not fully awake, often with no memory of the event. If a patient experiences such an episode, it should be reported to his or her doctor immediately, since “sleep-driving” can be dangerous. This behavior is more likely to occur when temazepam capsules are taken with alcohol or other central nervous system depressants (see WARNINGS). Other complex behaviors (e.g., preparing and eating food, making phone calls, or having sex) have been reported in patients who are not fully awake after taking a sedative-hypnotic. As with “sleep-driving”, patients usually do not remember these events.

Advise patients that increased drowsiness and decreased consciousness may increase the risk of falls in some patients.

Pregnancy
Advise pregnant females that use of temazepam capsules late in pregnancy can result in sedation (respiratory depression, lethargy, hypotonia) and/or withdrawal symptoms (hyperreflexia, irritability, restlessness, tremors, inconsolable crying, and feeding difficulties) in newborns (see WARNINGS, Neonatal Sedation and Withdrawal Syndromeand PRECAUTIONS, Pregnancy). Instruct patients to inform their healthcare provider if they are pregnant.

Advise patients that there is a pregnancy exposure registry that monitors pregnancy outcomes in women exposed to temazepam capsules during pregnancy (see PRECAUTIONS, Pregnancy).

Nursing
Instruct patients to notify their healthcare provider if they are breastfeeding or intend to breastfeed. Instruct breastfeeding patients using temazepam capsules to monitor infants for excessive sedation, poor feeding and poor weight gain, and to seek medical attention if they notice these signs (see PRECAUTIONS, Nursing Mothers).

Laboratory Tests

The usual precautions should be observed in patients with impaired renal or hepatic function and in patients with chronic pulmonary insufficiency. Abnormal liver function tests as well as blood dyscrasias have been reported with benzodiazepines.

Drug Interactions

The concomitant use of benzodiazepines and opioids increases the risk of respiratory depression because of actions at different receptor sites in the CNS that control respiration. Benzodiazepines interact at GABAA sites and opioids interact primarily at mu receptors. When benzodiazepines and opioids are combined, the potential for benzodiazepines to significantly worsen opioid-related respiratory depression exists. Limit dosage and duration of concomitant use of benzodiazepines and opioids, and monitor patients closely for respiratory depression and sedation.

The benzodiazepines, including temazepam, produce additive CNS-depressant effects when co-administered with other CNS depressants such as alcohol, barbiturates, antipsychotics, sedative/hypnotics, anxiolytics, antidepressants, narcotic analgesics, sedative antihistamines, anticonvulsants, and anesthetics.

The pharmacokinetic profile of temazepam does not appear to be altered by orally administered cimetidine dosed according to labeling.

Carcinogenesis, Mutagenesis, Impairment of Fertility

Carcinogenicity studies were conducted in rats at dietary temazepam doses up to 160 mg/kg/day for 24 months and in mice at dietary doses of 160 mg/kg/day for 18 months. No evidence of carcinogenicity was observed although hyperplastic liver nodules were observed in female mice exposed to the highest dose. The clinical significance of this finding is not known.

Fertility in male and female rats was not adversely affected by temazepam capsules.

No mutagenicity tests have been done with temazepam.

Pregnancy

Pregnancy Exposure Registry
There is a pregnancy registry that monitors pregnancy outcomes in women exposed to psychiatric medications, including temazepam capsules, during pregnancy. Healthcare providers are encouraged to register patients by calling the National Pregnancy Registry for Psychiatric Medications at 1-866-961-2388 or visiting online at https://womensmentalhealth.org/pregnancyregistry/.

Risk Summary
Neonates born to mothers using benzodiazepines late in pregnancy have been reported to experience symptoms of sedation and/or neonatal withdrawal (see WARNINGS, Neonatal Sedation and Withdrawal Syndromeand Clinical Considerations). Available data from published observational studies of pregnant women exposed to benzodiazepines do not report a clear association with benzodiazepines and major birth defects (see Data).

The background risk of major birth defects and miscarriage for the indicated population is unknown. All pregnancies have a background risk of birth defect, loss, or other adverse outcomes. In the U.S. general population, the estimated risk of major birth defects and of miscarriage in clinically recognized pregnancies is 2% to 4% and 15% to 20%, respectively.

Clinical Considerations
Fetal/Neonatal Adverse Reactions
Benzodiazepines cross the placenta and may produce respiratory depression, hypotonia and sedation in neonates. Monitor neonates exposed to temazepam capsules during pregnancy or labor for signs of sedation, respiratory depression, hypotonia, and feeding problems. Monitor neonates exposed to temazepam capsules during pregnancy for signs of withdrawal. Manage these neonates accordingly (see WARNINGS, Neonatal Sedation and Withdrawal Syndrome).

Data
Human Data
Published data from observational studies on the use of benzodiazepines during pregnancy do not report a clear association with benzodiazepines and major birth defects. Although early studies reported an increased risk of congenital malformations with diazepam and chlordiazepoxide, there was no consistent pattern noted. In addition, the majority of more recent case-control and cohort studies of benzodiazepine use during pregnancy, which were adjusted for confounding exposures to alcohol, tobacco and other medications, have not confirmed these findings.

Animal Data
Reproduction studies in animals with temazepam were performed in rats and rabbits. In a perinatal-postnatal study in rats, oral doses of 60 mg/kg/day resulted in increasing nursling mortality. Teratology studies in rats demonstrated increased fetal resorptions at doses of 30 and 120 mg/kg in one study and increased occurrence of rudimentary ribs, which are considered skeletal variants, in a second study at doses of 240 mg/kg or higher. In rabbits, occasional abnormalities such as exencephaly and fusion or asymmetry of ribs were reported without dose relationship. Although these abnormalities were not found in the concurrent control group, they have been reported to occur randomly in historical controls. At doses of 40 mg/kg or higher, there was an increased incidence of the 13th rib variant when compared to the incidence in concurrent and historical controls.

Nursing Mothers

Risk Summary
Temazepam is present in breast milk. There are reports of sedation, poor feeding and poor weight gain in infants exposed to benzodiazepines through breast milk. The effects of temazepam on milk production are unknown.

The developmental and health benefits of breastfeeding should be considered along with the mother’s clinical need for temazepam capsules and any potential adverse effects on the breastfed infant from temazepam capsules or from the underlying maternal condition.

Clinical Considerations
Infants exposed to temazepam capsules through breast milk should be monitored for sedation, poor feeding and poor weight gain.

Pediatric Use

Safety and effectiveness in pediatric patients have not been established.

Geriatric Use

Clinical studies of Restoril did not include sufficient numbers of subjects aged 65 and over to determine whether they respond differently from younger subjects. Other reported clinical experience has not identified differences in response between the elderly and younger patients. In general, dose selection for an elderly patient should be cautious, usually starting at the low end of the dosing range, reflecting the greater frequency of decreased hepatic, renal, or cardiac function, and of concomitant disease or other drug therapy commonly observed in this population. Temazepam capsules 7.5 mg is recommended as the initial dosage for patients aged 65 and over since the risk of the development of oversedation, dizziness, confusion, ataxia and/or falls increases substantially with larger doses of benzodiazepines in elderly and debilitated patients.

ADVERSE REACTIONS

During controlled clinical studies in which 1076 patients received temazepam capsules at bedtime, the drug was well tolerated. Side effects were usually mild and transient. Adverse reactions occurring in 1% or more of patients are presented in the following table:

 | Temazepam Capsules % Incidence (n=1076) | Placebo % Incidence (n=783)
Drowsiness | 9.1 | 5.6
Headache | 8.5 | 9.1
Fatigue | 4.8 | 4.7
Nervousness | 4.6 | 8.2
Lethargy | 4.5 | 3.4
Dizziness | 4.5 | 3.3
Nausea | 3.1 | 3.8
Hangover | 2.5 | 1.1
Anxiety | 2.0 | 1.5
Depression | 1.7 | 1.8
Dry Mouth | 1.7 | 2.2
Diarrhea | 1.7 | 1.1
Abdominal Discomfort | 1.5 | 1.9
Euphoria | 1.5 | 0.4
Weakness | 1.4 | 0.9
Confusion | 1.3 | 0.5
Blurred Vision | 1.3 | 1.3
Nightmares | 1.2 | 1.7
Vertigo | 1.2 | 0.8

The following adverse events have been reported less frequently (0.5% to 0.9%):

Central Nervous System –anorexia, ataxia, equilibrium loss, tremor, increased dreaming

Cardiovascular –dyspnea, palpitations

Gastrointestinal –vomiting

Musculoskeletal –backache

Special Senses –hyperhidrosis, burning eyes

Amnesia, hallucinations, horizontal nystagmus, and paradoxical reactions including restlessness, overstimulation and agitation were rare (less than 0.5%).

DRUG ABUSE AND DEPENDENCE

Controlled Substance

Temazepam capsules contain temazepam, a Schedule IV controlled substance.

Abuse

Temazepam capsules are a benzodiazepine and a CNS depressant with a potential for abuse and addiction. Abuse is the intentional, non-therapeutic use of a drug, even once, for its desirable psychological or physiological effects. Misuse is the intentional use, for therapeutic purposes, of a drug by an individual in a way other than prescribed by a healthcare provider or for whom it was not prescribed.

Drug addiction is a cluster of behavioral, cognitive, and physiological phenomena that may include a strong desire to take the drug, difficulties in controlling drug use (e.g., continuing drug use despite harmful consequences, giving a higher priority to drug use than other activities and obligations), and possible tolerance or physical dependence. Even taking benzodiazepines as prescribed may put patients at risk for abuse and misuse of their medication. Abuse and misuse of benzodiazepines may lead to addiction.

Abuse and misuse of benzodiazepines often (but not always) involve the use of doses greater than the maximum recommended dosage and commonly involve concomitant use of other medications, alcohol, and/or illicit substances, which is associated with an increased frequency of serious adverse outcomes, including respiratory depression, overdose, or death. Benzodiazepines are often sought by individuals who abuse drugs and other substances, and by individuals with addictive disorders (see WARNINGS, Abuse, Misuse, and Addiction).

The following adverse reactions have occurred with benzodiazepine abuse and/or misuse: abdominal pain, amnesia, anorexia, anxiety, aggression, ataxia, blurred vision, confusion, depression, disinhibition, disorientation, dizziness, euphoria, impaired concentration and memory, indigestion, irritability, muscle pain, slurred speech, tremors, and vertigo.

The following severe adverse reactions have occurred with benzodiazepine abuse and/or misuse: delirium, paranoia, suicidal ideation and behavior, seizures, coma, breathing difficulty, and death. Death is more often associated with polysubstance use (especially benzodiazepines with other CNS depressants such as opioids and alcohol).

Dependence

Physical Dependence
Temazepam capsules may produce physical dependence from continued therapy. Physical dependence is a state that develops as a result of physiological adaptation in response to repeated drug use, manifested by withdrawal signs and symptoms after abrupt discontinuation or a significant dose reduction of a drug. Abrupt discontinuation or rapid dosage reduction of benzodiazepines or administration of flumazenil, a benzodiazepine antagonist, may precipitate acute withdrawal reactions, including seizures, which can be life-threatening. Patients at an increased risk of withdrawal adverse reactions after benzodiazepine discontinuation or rapid dosage reduction include those who take higher dosages (i.e., higher and/or more frequent doses) and those who have had longer durations of use (see WARNINGS, Dependence and Withdrawal Reactions).

To reduce the risk of withdrawal reactions, use a gradual taper to discontinue temazepam capsules or reduce the dosage (see DOSAGE AND ADMINISTRATION, Discontinuation or Dosage Reduction of Temazepam Capsulesand WARNINGS, Dependence and Withdrawal Reactions).

Acute Withdrawal Signs and Symptoms
Acute withdrawal signs and symptoms associated with benzodiazepines have included abnormal involuntary movements, anxiety, blurred vision, depersonalization, depression, derealization, dizziness, fatigue, gastrointestinal adverse reactions (e.g., nausea, vomiting, diarrhea, weight loss, decreased appetite), headache, hyperacusis, hypertension, irritability, insomnia, memory impairment, muscle pain and stiffness, panic attacks, photophobia, restlessness, tachycardia, and tremor. More severe acute withdrawal signs and symptoms, including life-threatening reactions, have included catatonia, convulsions, delirium tremens, depression, hallucinations, mania, psychosis, seizures, and suicidality.

Protracted Withdrawal Syndrome
Protracted withdrawal syndrome with benzodiazepines is characterized by anxiety, cognitive impairment, depression, insomnia, formication, motor symptoms (e.g., weakness, tremor, muscle twitches), paresthesia, and tinnitus that persists beyond 4 to 6 weeks after initial benzodiazepine withdrawal. Protracted withdrawal symptoms may last weeks to more than 12 months. As a result, there may be difficulty in differentiating withdrawal symptoms from potential re-emergence or continuation of symptoms for which the benzodiazepine was being used.

Tolerance
Tolerance to temazepam capsules may develop from continued therapy. Tolerance is a physiological state characterized by a reduced response to a drug after repeated administration (i.e., a higher dose of a drug is required to produce the same effect that was once obtained at a lower dose). Tolerance to the therapeutic effect of temazepam capsules may develop; however, little tolerance develops to the amnestic reactions and other cognitive impairments caused by benzodiazepines.

OVERDOSAGE

Overdosage of benzodiazepines is characterized by central nervous system depression ranging from drowsiness to coma. In mild to moderate cases, symptoms can include drowsiness, confusion, dysarthria, lethargy, hypnotic state, diminished reflexes, ataxia, and hypotonia. Rarely, paradoxical or disinhibitory reactions (including agitation, irritability, impulsivity, violent behavior, confusion, restlessness, excitement, and talkativeness) may occur. In severe overdosage cases, patients may develop respiratory depression and coma. Overdosage of benzodiazepines in combination with other CNS depressants (including alcohol and opioids) may be fatal (see WARNINGS, Abuse, Misuse, and Addiction). Markedly abnormal (lowered or elevated) blood pressure, heart rate, or respiratory rate raise the concern that additional drugs and/or alcohol are involved in the overdosage.

In managing benzodiazepine overdosage, employ general supportive measures, including intravenous fluids and airway management. Flumazenil, a specific benzodiazepine receptor antagonist indicated for the complete or partial reversal of the sedative effects of benzodiazepines in the management of benzodiazepine overdosage, can lead to withdrawal and adverse reactions, including seizures, particularly in the context of mixed overdosage with drugs that increase seizure risk (e.g., tricyclic and tetracyclic antidepressants) and in patients with long-term benzodiazepine use and physical dependency. The risk of withdrawal seizures with flumazenil use may be increased in patients with epilepsy. Flumazenil is contraindicated in patients who have received a benzodiazepine for control of a potentially life-threatening condition (e.g., status epilepticus). If the decision is made to use flumazenil, it should be used as an adjunct to, not as a substitute for, supportive management of benzodiazepine overdosage. See the flumazenil injection Prescribing Information.

Consider contacting the Poison Help line (1-800-221-2222) or a medical toxicologist for additional overdosage management recommendations.

DOSAGE AND ADMINISTRATION

While the recommended usual adult dose is 15 mg before retiring, 7.5 mg may be sufficient for some patients, and others may need 30 mg. In transient insomnia, a 7.5 mg dose may be sufficient to improve sleep latency. In elderly or debilitated patients, it is recommended that therapy be initiated with 7.5 mg until individual responses are determined.

Discontinuation or Dosage Reduction of Temazepam Capsules

To reduce the risk of withdrawal reactions, use a gradual taper to discontinue temazepam capsules or reduce the dosage. If a patient develops withdrawal reactions, consider pausing the taper or increasing the dosage to the previous tapered dosage level. Subsequently decrease the dosage more slowly (see WARNINGS, Dependence and Withdrawal Reactionsand DRUG ABUSE AND DEPENDENCE: Dependence).

HOW SUPPLIED

Temazepam Capsules USP
7.5 mg
Blue and pink capsules, with the pink body imprinted “FOR SLEEP” on one side and on the other side in red, and a blue cap imprinted “7.5 mg” twice in red.
Unit dose packages of 30 (3 x 10) NDC 68084-549-21

Storage: Store at 20° to 25°C (68° to 77°F) [see USP Controlled Room Temperature].

FOR YOUR PROTECTION: Do not use if blister is torn or broken.

Mallinckrodt, the “M” brand mark, the Mallinckrodt Pharmaceuticals logo, and other brands are trademarks of a Mallinckrodt company.

© 2023 Mallinckrodt.

PACKAGING INFORMATION

American Health Packaging unit dose blisters (see How Supplied section) contain drug product from SpecGx LLC. as follows:
(7.5 mg / 30 UD) NDC 68084-549-21 packaged from NDC 0406-9960

Distributed by:
American Health Packaging
Columbus, OH 43217

8254921/1123

To order more Medication Guides call American Health Packaging at 1-800-707-4621.

MEDICATION GUIDE

8254921/1123
Temazepam (te-maz'ĕ-pam) Capsules, C-IV

What is the most important information I should know about temazepam capsules?

- Temazepam capsules are a benzodiazepine medicine. Taking benzodiazepines with opioid medicines, alcohol, or other central nervous system (CNS) depressants (including street drugs) can cause severe drowsiness, breathing problems (respiratory depression), coma and death. Get emergency help right away if any of the following happens:
- shallow or slowed breathing
- breathing stops (which may lead to the heart stopping)
- excessive sleepiness (sedation)
- Do not drive or operate heavy machinery until you know how taking temazepam capsules and opioids affects you.
- Risk of abuse, misuse, and addiction. There is a risk of abuse, misuse, and addiction with benzodiazepines including temazepam capsules which can lead to overdose and serious side effects including coma and death.
- Serious side effects including coma and death have happened in people who have abused or misused benzodiazepines, including temazepam capsules. These serious side effects may also include delirium, paranoia, suicidal thoughts or actions, seizures, and difficulty breathing. Call your healthcare provider or go to the nearest hospital emergency room right away if you get any of these serious side effects.
- You can develop an addiction even if you take temazepam capsules as prescribed by your healthcare provider.
- Take temazepam capsules exactly as your healthcare provider prescribed.
- Do not share your temazepam capsules with other people.
- Keep temazepam capsules in a safe place and away from children.
- Physical dependence and withdrawal reactions. Temazepam capsules can cause physical dependence and withdrawal reactions.
- Do not suddenly stop taking temazepam capsules. Stopping temazepam capsules suddenly can cause serious and life-threatening side effects, including, unusual movements, responses, or expressions, seizures, sudden and severe mental or nervous system changes, depression, seeing or hearing things that others do not see or hear, an extreme increase in activity or talking, losing touch with reality, and suicidal thoughts or actions. Call your healthcare provider or go to the nearest hospital emergency room right away if you get any of these symptoms.
- Some people who suddenly stop benzodiazepines have symptoms that can last for several weeks to more than 12 months, including, anxiety, trouble remembering, learning, or concentrating, depression, problems sleeping, feeling like insects are crawling under your skin, weakness, shaking, muscle twitching, burning or prickling feeling in your hands, arms, legs or feet, and ringing in your ears.
- Physical dependence is not the same as drug addiction. Your healthcare provider can tell you more about the differences between physical dependence and drug addiction.
- Do not take more temazepam capsules than prescribed or take temazepam capsules for longer than prescribed.
- After taking temazepam capsules, you may get up out of bed while not being fully awake and do an activity that you do not know you are doing. The next morning, you may not remember that you did anything during the night. You have a higher chance for doing these activities if you drink alcohol or take other medicines that make you sleepy with temazepam capsules. Reported activities include:
- driving a car (“sleep-driving”)
- making and eating food
- talking on the phone
- having sex
- sleep-walking

Call your healthcare provider right away if you find out that you have done any of the above activities after taking temazepam capsules.

What are temazepam capsules?

- Temazepam capsules are a prescription sleep medicine. Temazepam capsules are used in adults for the short-term (usually 7 to 10 days) treatment of a sleep problem called insomnia. Symptoms of insomnia include trouble falling asleep and waking up often during the night.
- Temazepam capsules are a federal controlled substance (C-IV) because it contains temazepam that can be abused or lead to dependence. Keep temazepam capsules in a safe place to prevent misuse and abuse. Selling or giving away temazepam capsules may harm others, and is against the law. Tell your healthcare provider if you have ever abused or been dependent on alcohol, prescription medicines or street drugs.
- It is not known if temazepam capsules are safe and effective in children.
- It is not known if temazepam capsules are safe and effective for use longer than 2 weeks.

Do not take temazepam capsules if you

- are allergic to temazepam or any of the ingredients in temazepam capsules. See the end of this Medication Guide for a complete list of ingredients in temazepam capsules.

Before you take temazepam capsules, tell your healthcare provider about all of your medical conditions, including if you:

- have a history of depression, mental illness or, suicidal thoughts
- have a history of drug or alcohol abuse or addiction
- have lung disease or breathing problems
- are pregnant or plan to become pregnant.
  - Taking temazepam capsules late in pregnancy may cause your baby to have symptoms of sedation (breathing problems, sluggishness, low muscle tone), and/or withdrawal symptoms (jitteriness, irritability, restlessness, shaking, excessive crying, feeding problems).
  - Tell your healthcare provider right away if you become pregnant or think you are pregnant during treatment with temazepam capsules.
  - There is a pregnancy registry for women who take temazepam capsules during pregnancy. The purpose of the registry is to collect information about the health of women and their babies exposed to temazepam capsules. If you become pregnant during treatment with temazepam capsules, talk to your healthcare provider about registering with the National Pregnancy Registry for Psychiatric Medications. You can register by calling 1-866-961-2388 or visiting https://womensmentalhealth.org/research/pregnancyregistry/.
- are breastfeeding, or plan to breastfeed. Temazepam can pass through your breast milk.
  - Breastfeeding during treatment with temazepam capsules may cause your baby to have sleepiness, feeding problems, and decreased weight gain.
  - Talk to your healthcare provider about the best way to feed your baby if you take temazepam capsules.

Tell your healthcare provider about all of the medicines you take, including prescription and over-the-counter medicines, vitamins, and herbal supplements.

Taking temazepam capsules with certain other medicines can cause side effects or affect how well temazepam capsules or the other medicines work. Do not start or stop other medicines without talking to your healthcare provider.

Do not take temazepam capsules with other medicines that can make you sleepy unless your healthcare provider tells you to.

How should I take temazepam capsules?

- See “What is the most important information I should know about temazepam capsules?”
- Take temazepam capsules exactly as your healthcare providers tell you to take it. Take temazepam capsules right before you get into bed.
- Do not take temazepam capsules unless you are able to get a full night’s sleep before you must be active again.
- If you take too much temazepam capsules or overdose, get emergency treatment right away.

What are the possible side effects of temazepam capsules?

Temazepam capsules may cause serious side effects, including:

- See “What is the most important information I should know about temazepam capsules?”
- Abnormal thoughts and behavior. Symptoms include more outgoing or aggressive behavior than normal, confusion, agitation, hallucinations, worsening of depression, and suicidal thoughts.
- Severe allergic reactions. Symptoms include swelling of the tongue or throat, trouble breathing, and nausea and vomiting. Get emergency medical help right away if you have these symptoms after taking temazepam capsules.
  - Temazepam capsules can make you sleepy or dizzy and can slow your thinking and motor skills. Do not drive, operate heavy machinery, or do other dangerous activities until you know how temazepam capsules affect you.
  - Do not drink alcohol or take other drugs that may make you sleepy or dizzy while taking temazepam capsules without first talking to your healthcare provider. When taken with alcohol or other drugs that cause sleepiness or dizziness, temazepam capsules may make your sleepiness or dizziness much worse.

The most common side effects of temazepam capsules include:

- drowsiness
- headache
- tiredness
- nervousness
- dizziness
- nausea

You may still feel drowsy the next day after taking temazepam capsules. Do not drive or do other dangerous activities after taking temazepam capsules until you feel fully awake.
These are not all the possible side effects of temazepam capsules. Call your doctor for medical advice about side effects. You may report side effects to FDA at 1-800-FDA-1088.

How should I store temazepam capsules?

- Store temazepam capsules at room temperature between 68°F to 77°F (20°C to 25°C).
- Keep temazepam capsules and all medicines out of the reach of children.

General information about the safe and effective use of temazepam capsules.
Medicines are sometimes prescribed for purposes other than those listed in a Medication Guide. Do not use temazepam capsules for a condition for which it was not prescribed. Do not give temazepam capsules to other people, even if they have the same symptoms that you have. It may harm them. You can ask your healthcare provider or pharmacist for information about temazepam capsules that is written for healthcare professionals.

What are the ingredients in temazepam capsules?
Active Ingredient:temazepam
Inactive Ingredients: gelatin, lactose, magnesium stearate, red iron oxide, titanium dioxide

If you would like more information about the drug product, call Mallinckrodt Inc. at 1-800-778-7898 or visit www.mallinckrodt.com.
For more information about the packaging or labeling, call American Health Packaging at 1-800-707-4621.

This Medication Guide has been approved by the U.S. Food and Drug Administration

Distributed by:
American Health Packaging
Columbus, OH 43217

8254921/1123

Package/Label Display Panel – Carton – 7.5 mg

NDC 68084- 549-21

Temazepam
Capsules USP CIV

7.5 mg

30 Capsules (3 x 10) Rx Only

PHARMACIST: Dispense with Medication Guide to each patient.

Each Capsule Contains:
Temazepam USP .................................................................7.5 mg

Usual Dosage: See package insert for full prescribing information.

Store at 20° to 25°C (68° to 77°F); excursions permitted between
15° to 30°C (59° to 86°F) [see USP Controlled Room Temperature].

FOR YOUR PROTECTION: Do not use if blister is torn or broken.

The drug product contained in this package is from
NDC # 0406-9960, SpecGx LLC.

Distributed by: American Health Packaging, Columbus, Ohio 43217

054921
0254921/1123

Package/Label Display Panel – Blister – 7.5 mg

Temazepam
Capsule USP CIV

7.5 mg